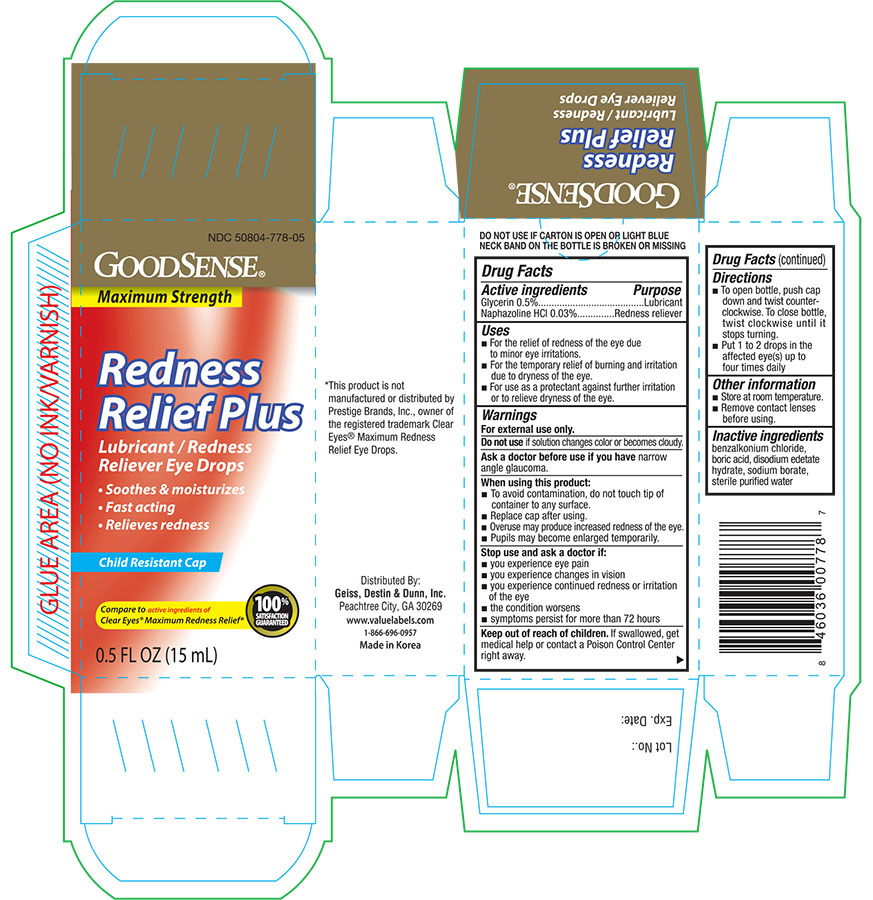 DRUG LABEL: Goodsense Maximum Strength Redness Relief Plus
NDC: 50804-778 | Form: SOLUTION/ DROPS
Manufacturer: Good Sense (Geiss, destin & dunn, Inc.)
Category: otc | Type: HUMAN OTC DRUG LABEL
Date: 20160108

ACTIVE INGREDIENTS: GLYCERIN .00015 mg/1 mL; NAPHAZOLINE HYDROCHLORIDE .0025 mg/1 mL
INACTIVE INGREDIENTS: BENZALKONIUM CHLORIDE; BORIC ACID; EDETATE DISODIUM; SODIUM BORATE; WATER

Active ingredients Purpose

Glycerin 0.5%.........................................................Lubricant

Naphazoline HCL 0.03%..................................Redness reliever

Uses

- For the relief of redness of the eye due to minor eye irritations.
- For the temporary relief of burning and irritation due to dryness of the eye.
- For use as a protectant against further irritation or to relieve dryness of the eye.

Warnings

For external use only.

Do not use if solution changes color or becomes cloudy.

Ask a doctor before use if you have narrow angle glaucoma.

When using this product:

- To avoid contamination, do not touch tip of container to any surface.
- Replace cap after using.
- Overuse may produce increased redness of the eye.
- Pupils may become enlarged temporarily.

Stop use and ask a doctor if:

- you experience eye pain
- you experience changes in vision
- you experience continued redness or irritation of the eye
- the condition worsens
- symptoms persist for more than 72 hours

Keep out of reach of children.

If swallowed, get medical help or contact a Poision Control Center right away.

Directions

- To open bottle, push cap down and twist counter-clockwise. To close bottle, twist clockwise until it stops turning.
- Put 1 to 2 drops in the affected eye(s) up to four time daily

Other information

- Store at room temperature.
- Remove contact lenses before using.

Inactive ingredients

benzalkonium chloride, boric acid, disodium edetate hydrate, sodium borate, sterile purified water

DOSAGE AND ADMINISTRATION

Distributed By:

Geiss, Destin & Dunn, Inc.

Peachtree City, GA 30269

www.valuelabels.com

Made in Korea